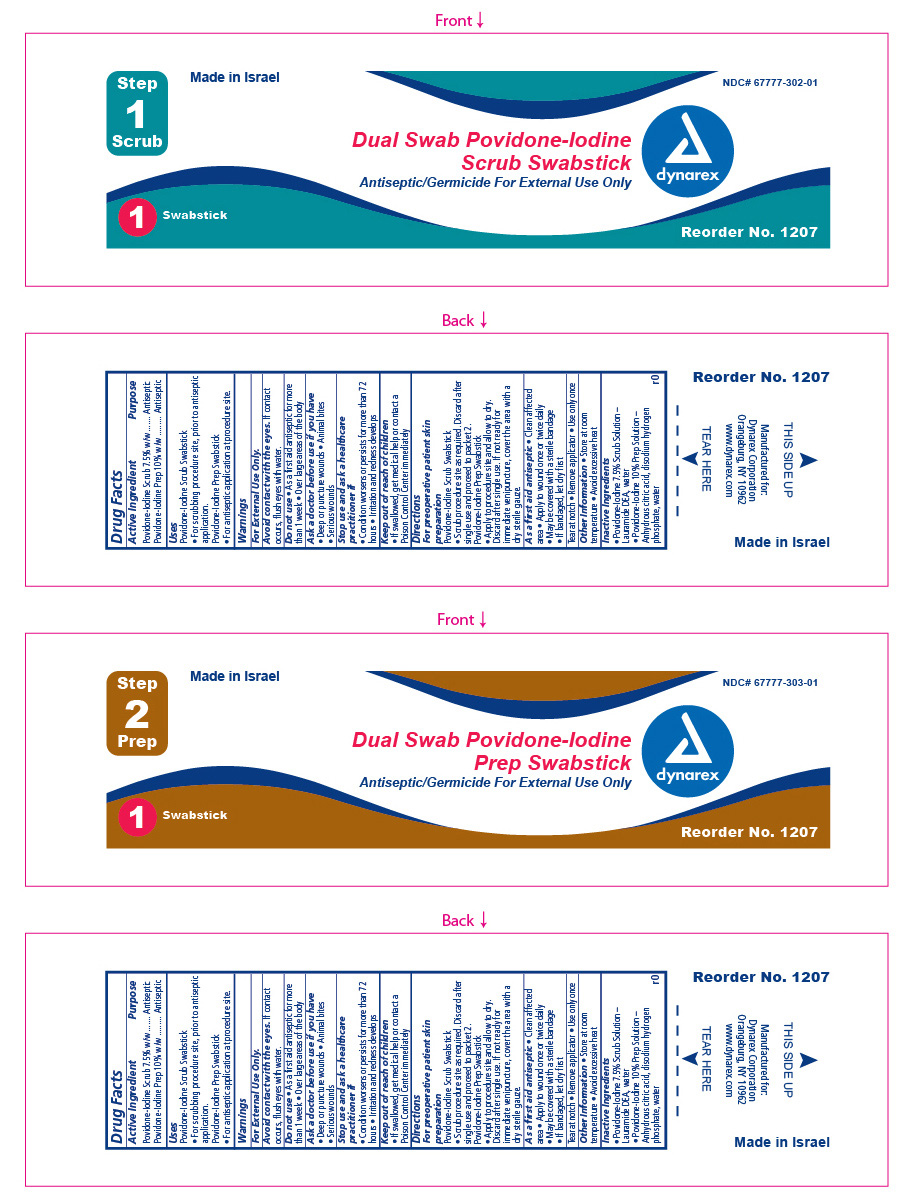 DRUG LABEL: Dual Swab Povidone-Iodine Prep
NDC: 67777-414 | Form: KIT | Route: TOPICAL
Manufacturer: Dynarex Corporation
Category: otc | Type: HUMAN OTC DRUG LABEL
Date: 20200124

ACTIVE INGREDIENTS: POVIDONE-IODINE 7.5 mg/1 mL; POVIDONE-IODINE 10 mg/1 mL
INACTIVE INGREDIENTS: LAURIC DIETHANOLAMIDE; WATER; ANHYDROUS CITRIC ACID; SODIUM PHOSPHATE, DIBASIC DODECAHYDRATE; WATER

1205 Dynarex Dual Prep and Scrub Swabstick NDC 67777-302-01

Active Ingredient Purpose

Povidone Iodine Scrub 7.5% w/w Antiseptic

Povidone Iodine Prep 10% w/w Antiseptic

Purpose

Uses

Povidone Iodine Scrub Swabstick - For scrubbing procedure site, prior to antiseptic application.

Povidone Iodine Prep Swabstick - For antiseptic application at procedure site.

Indications and Usage

- For pre-operative patient skin preparation.

Warnings

For External Use Only

Avoid contact with eyes. If contact occurs, flush with water.

Stop Use

Stop use and ask a healthcare professional if;

- condition worsens or persists for more than 72 hours
- if pain, irritation, redness or swelling occurs

Ask a doctor before use if you have:

- deep puncture wounds
- animal bites
- serious wounds

Do Not Use:

- as a first aid antiseptic for more than 1 week
- over large areas of the body

Keep Out Of Reach Of Children

- if swallowed, get medical help or contact a Poison Control Center immediately .

Dosage and Administration

Directions

For pre-operative patient skin preparation:

- Apply to procedure site and allow to dry.
- discard after single use.
- If not ready for immediate venipuncture, cover the area with a dry sterile gauze.

As a first aid antiseptic:

- clean affected area
- apply to wound once or twice daily
- may be covered with a sterile bandage
- if bandaged let dry first

Tear at notch, remove applicator, use only once.

Inactive Ingredients

- Povidone Iodine 7.5% Scrub Solution - Lauramide DEA, water
- Povidone Iodine 10% Prep Solution - Anhydrous citric acid, disodium hydrogen phosphate, water

Other information

- Store at room temperature
- Avoid excessive heat

Principal Display panel

Dynarex Dual Swab Prep and Scrub Kit

Item 1207

1207_pouches.jpg